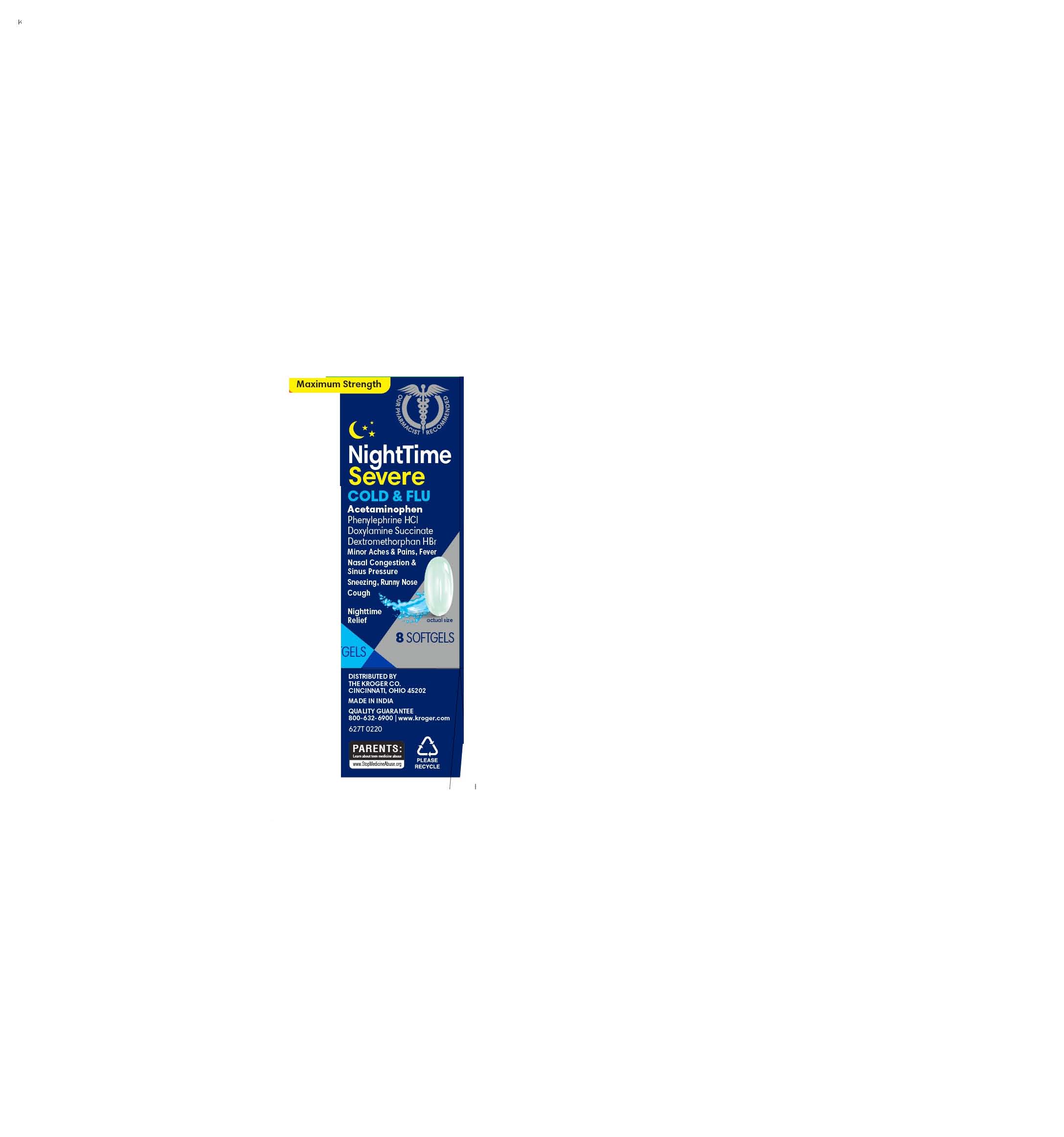 DRUG LABEL: NIGHTTIME SEVERE COLD AND FLU
NDC: 41226-626 | Form: CAPSULE, LIQUID FILLED
Manufacturer: KROGER
Category: otc | Type: HUMAN OTC DRUG LABEL
Date: 20251229

ACTIVE INGREDIENTS: DEXTROMETHORPHAN HYDROBROMIDE 10 mg/1 1; ACETAMINOPHEN 325 mg/1 1; DOXYLAMINE SUCCINATE 6.25 mg/1 1; PHENYLEPHRINE HYDROCHLORIDE 5 mg/1 1
INACTIVE INGREDIENTS: POLYETHYLENE GLYCOL, UNSPECIFIED; SHELLAC; GLYCERIN; FD&C BLUE NO. 1; GELATIN; WATER; SORBITOL; TITANIUM DIOXIDE

KROGER 626T NIGHTTME SEVERE COLD AND FLU

ACTIVE INGREDIENT

- Acetaminophen
- PhenylephrineHCl,
- Doxylamine Succinate
- Dextromethorphan HBr

INACTIVE INGREDIENT

FD&C BLUE #1, GELATN, GLYCERIN, POLYETHYLENE GLYCOL, POVIDONE, PROPYLENE GLYCOL, PURIFIED WATER, SHELLAC, SORBITOL SORBITAN SOLUTION, TITANIUM DIOXIDE

PURPOSE

- Pain reliever/Fever reducer
- Cough suppressant
- Antihistamine
- Nasal decongestant

INDICATIONS AND USAGE

temporarily relieves common cold/flu symptoms:

nasal congestion
sinus congestion & pressure
cough due to minor throat & bronchial irritation
cough to help you sleep
minor aches & pains
headache
fever
sore throat
runny nose & sneezing
reduces swelling of nasal passages
temporarily restores freer breathing through the nose
promotes nasal and/or sinus drainage

DOSAGE AND ADMINISTRATION

take only as directed
do not exceed 8 Softgels per 24 hours

- adults & children 12 yrs & over 2 Softgels with water every 6 hrs
- children 4 to under 12 yrs ask a doctor
- children under 4 yrs do not use

Keep out of reach of children.

In case of overdose, get medical help or contact a Poison Control Center right away (1-800-222-1222). Quick medical attention is critical for adults as well as for children even if you do not notice any signs or symptoms.

WARNINGS

Liver warning

This product contains acetaminophen.

Severe liver damage may occur if you take

more than 8 Softgels in 24 hrs, which is the maximum daily amount for this product
with other drugs containing acetaminophen
3 or more alcoholic drinks every day while using this product

Allergy Alert:

Acetaminophen may cause severe skin reactions. Symptoms may include:

Skin reddening
Blisters
Rash

If a skin reaction occurs, stop use and seek medical help right away

Sore throat warning

If sore throat is severe, persists for more than 2 days, is accompanied or followed by fever, headache, rash, nausea, or vomiting, consult a doctor promptly.